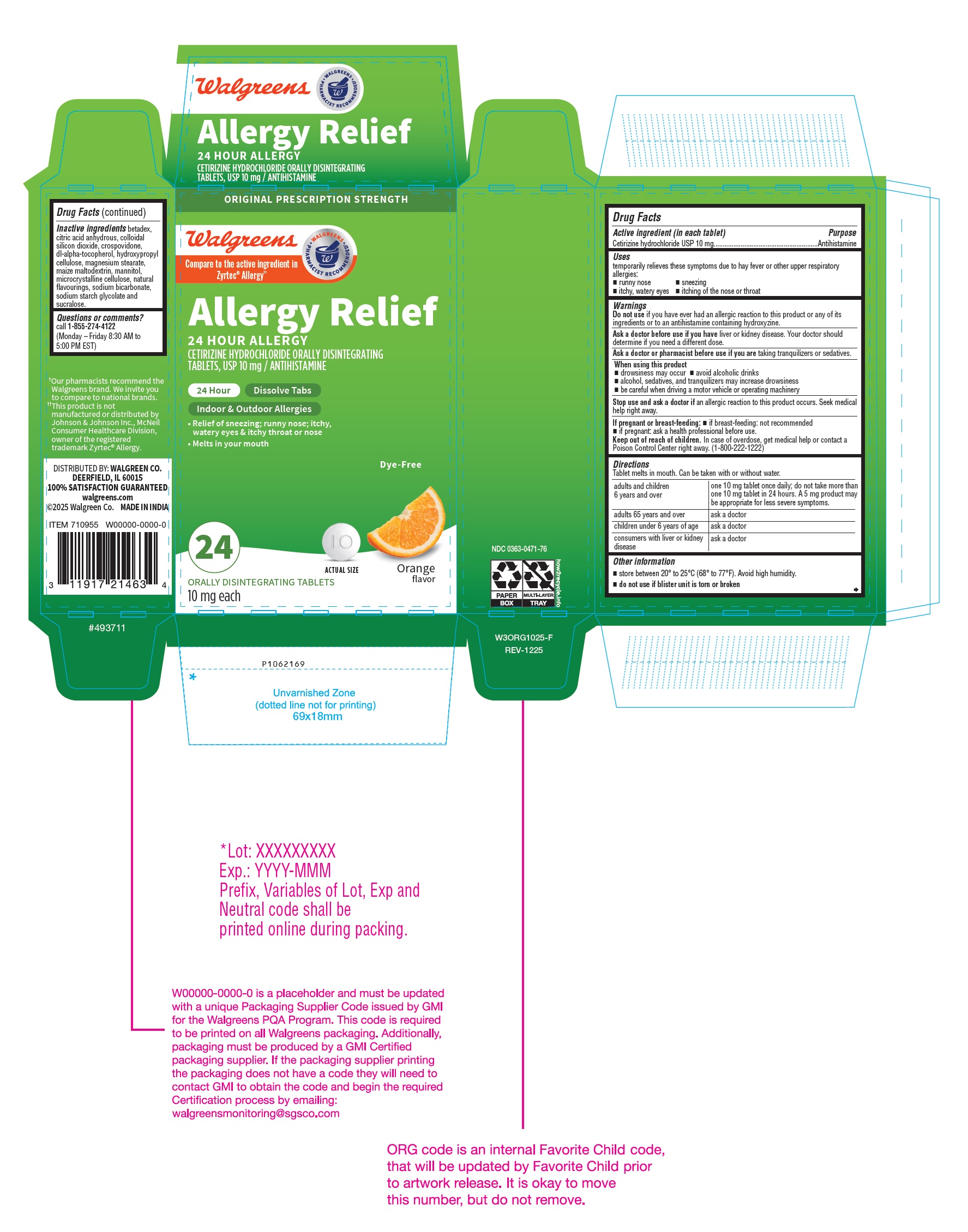 DRUG LABEL: Cetirizine Hydrochloride
NDC: 0363-0471 | Form: TABLET, ORALLY DISINTEGRATING
Manufacturer: WALGREEN CO.
Category: otc | Type: Human OTC Drug Label
Date: 20260108

ACTIVE INGREDIENTS: CETIRIZINE HYDROCHLORIDE 10 mg/1 1
INACTIVE INGREDIENTS: BETADEX; ANHYDROUS CITRIC ACID; SILICON DIOXIDE; CROSPOVIDONE (35 .MU.M); .ALPHA.-TOCOPHEROL, DL-; HYDROXYPROPYL CELLULOSE (110000 WAMW); MAGNESIUM STEARATE; MALTODEXTRIN; MANNITOL; MICROCRYSTALLINE CELLULOSE 101; MICROCRYSTALLINE CELLULOSE 102; SODIUM BICARBONATE; SODIUM STARCH GLYCOLATE TYPE A POTATO; SUCRALOSE

Drug Facts

Active ingredient (in each tablet)

Cetirizine hydrochloride USP 10 mg

Purpose

Antihistamine

Uses

temporarily relieves these symptoms due to hay fever or other upper respiratory allergies:

- runny nose
- sneezing
- itchy, watery eyes
- itching of the nose or throat

Do not use

if you have ever had an allergic reaction to this product or any of its ingredients or to an antihistamine containing hydroxyzine.

Ask a doctor before use if you have

liver or kidney disease. Your doctor should determine if you need a different dose.

Ask a doctor or pharmacist before use if you are

taking tranquilizers or sedatives.

When using this product

- drowsiness may occur
- avoid alcoholic drinks
- alcohol, sedatives, and tranquilizers may increase drowsiness
- be careful when driving a motor vehicle or operating machinery

Stop use and ask a doctor if

an allergic reaction to this product occurs. Seek medical help right away.

If pregnant or breast-feeding:

- if breast-feeding: not recommended
- if pregnant: ask a health professional before use.

Keep out of reach of children.

In case of overdose, get medical help or contact a Poison Control Center right away. (1-800-222-1222)

Directions

Tablet melts in mouth. Can be taken with or without water.

adults and children 6 years and over | one 10 mg tablet once daily; do not take more than one 10 mg tablet in 24 hours. A 5 mg product may be appropriate for less severe symptoms.
adults 65 years and over | ask a doctor
children under 6 years of age | ask a doctor
consumers with liver or kidney disease | ask a doctor

Other information

- store between 20° to 25°C (68° to 77°F). Avoid high humidity.
- do not use if blister unit is torn or broken

Inactive ingredients

betadex, citric acid anhydrous, colloidal silicon dioxide, crospovidone, dl-alpha-tocopherol, hydroxypropyl cellulose, magnesium stearate, maize maltodextrin, mannitol, microcrystalline cellulose, natural flavourings, sodium bicarbonate, sodium starch glycolate and sucralose.
Questions or comments?
call 1-855-274-4122 (Monday - Friday 8:30 AM to 5:00 PM EST)

DISTRIBUTED BY: WALGREEN CO.
DEERFIELD, IL 60015

MADE IN INDIA

PACKAGE LABEL-PRINCIPAL DISPLAY PANEL -10 mg (24 Orally Disintegrating Tablets) Blister Carton

ORIGINAL PRESCRIPTION STRENGTH
Walgreens
Compare to the active ingredient in
Zyrtec® Allergy††
Allergy Relief
24 HOUR ALLERGY
CETIRIZINE HYDROCHLORIDE ORALLY DISINTEGRATING
TABLETS, USP 10 mg / ANTIHISTAMINE
24 Hour Dissolve Tabs
Indoor & Outdoor Allergies

• Relief of sneezing; runny nose; itchy,
watery eyes & itchy throat or nose
• Melts in your mouth

Dye-Free

ACTUAL SIZE Orange
flavor
24
ORALLY DISINTEGRATING TABLETS
10 mg each